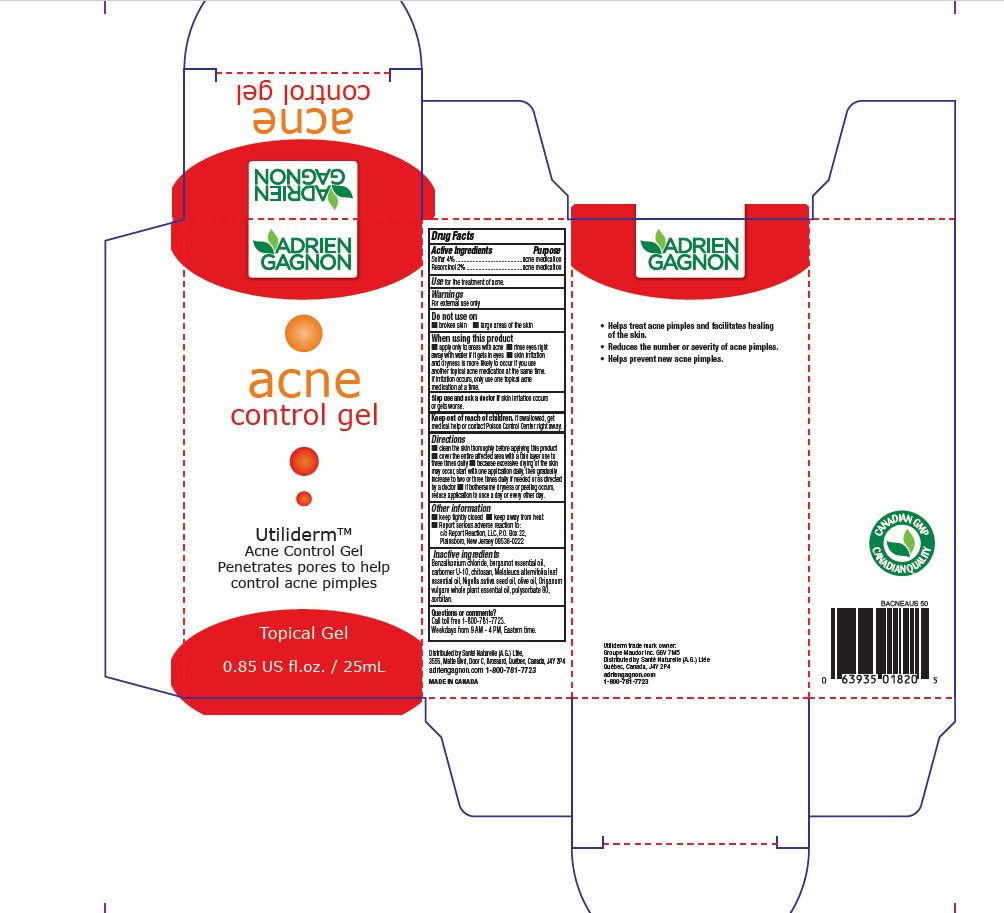 DRUG LABEL: Utiliderm Acne Control
NDC: 71493-001 | Form: GEL
Manufacturer: Sante Naturelle (A.G.) Ltee
Category: otc | Type: HUMAN OTC DRUG LABEL
Date: 20180324

ACTIVE INGREDIENTS: SULFUR 4 mg/100 mL; RESORCINOL 2 mg/100 mL
INACTIVE INGREDIENTS: BERGAMOT OIL; MELALEUCA ALTERNIFOLIA LEAF; NIGELLA SATIVA SEED OIL; OLIVE OIL; POLYSORBATE 80; SORBITAN; CHITOSAN MEDIUM MOLECULAR WEIGHT (200-400 MPA.S); BENZALKONIUM CHLORIDE; ORIGANUM VULGARE SUBSP. HIRTUM WHOLE; CARBOXYPOLYMETHYLENE

Utiliderm Acne Control Gel

Active Ingredients

Sulfur 4%

Resorcinol 2%

Purpose

acne medication

acne medication

Use

for the treatment of acne

Warnings

For external use only

Do not use on

■ broken skin ■ large areas of the skin

When using this product

■ apply only to areas with acne ■ rinse eyes right

away with water if it gets in eyes ■ skin irritation

and dryness is more likely to occur if you use

another topical acne medication at the same time.

If irritation occurs, only use one topical acne

medication at a time.

Stop use and ask a doctor if skin irritation occurs

or gets worse.

Keep out of reach of children. If swallowed, get

medical help or contact Poison Control Center right away.

Directions

■ clean the skin thoroughly before applying this product

■ cover the entire affected area with a thin layer one to

three times daily ■ because excessive drying of the skin

may occur, start with one application daily, then gradually

increase to two or three times daily if needed or as directed

by a doctor ■ if bothersome dryness or peeling occurs,

reduce application to once a day or every other day.

Other information

■ keep tightly closed ■ keep away from heat

■ Report serious adverse reaction to:

c/o Report Reaction, LLC, P.O. Box 22,

Plainsboro, New Jersey 08536-0222

Inactive ingredients

Benzalkonium chloride, bergamot essential oil,

carbomer U-10, chitosan, Melaleuca alternifolia leaf

essential oil, Nigella sativa seed oil, olive oil, Origanum

vulgare whole plant essential oil, polysorbate 80,

sorbitan.

Questions or comments?

Call toll free 1-800-781-7723.

Weekdays from 9 AM - 4 PM, Eastern time.